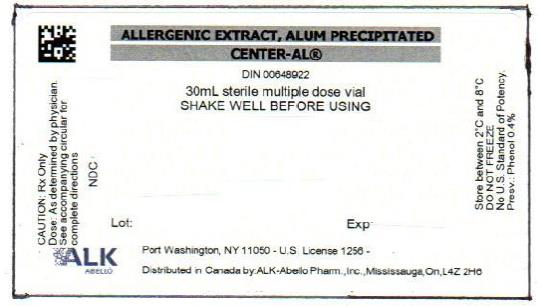 DRUG LABEL: 5 GRASS MIX
NDC: 0268-8005 | Form: INJECTION, SOLUTION
Manufacturer: ALK-Abello, Inc.
Category: other | Type: NON-STANDARDIZED ALLERGENIC LABEL
Date: 20230531

ACTIVE INGREDIENTS: PHLEUM PRATENSE POLLEN 1000 [PNU]/1 mL; DACTYLIS GLOMERATA POLLEN 1000 [PNU]/1 mL; POA PRATENSIS POLLEN 1000 [PNU]/1 mL; AGROSTIS GIGANTEA POLLEN 1000 [PNU]/1 mL; ANTHOXANTHUM ODORATUM POLLEN 1000 [PNU]/1 mL
INACTIVE INGREDIENTS: POTASSIUM ALUMINATE 0.05 g/1 mL; SODIUM HYDROXIDE 0.01 g/1 mL; PHENOL 0.004 mL/1 mL; SODIUM CHLORIDE 0.009 g/1 mL; HYDROCHLORIC ACID

Center- Al product mixtures

DIRECTIONS FOR USE OF CENTER - AL® THERAPEUTIC
ALLERGENIC EXTRACTS ALUM PRECIPITATED
OF
POLLENS, MOLDS,
INHALANTS AND EPIDERMALS
DOSAGE BASED ON
PROTEIN NITROGEN CONTENT

WARNING

This allergenic extract is intended for use by physicians who are experienced in the administration of allergenic extracts for immunotherapy and the emergency care of anaphylaxis, or for use under the guidance of an allergy specialist. These allergenic extracts are not directly interchangeable with allergenic extracts of the same labeled potency from different manufacturers. The patient must be re-evaluated with the newly selected extract. Patients being switched from other types of extracts such as aqueous extracts, glycerinated extracts, or alum precipitated extracts from other suppliers to this allergenic extract should be started as though they were coming under treatment for the first time. Patients should be instructed to recognize adverse reaction symptoms and cautioned to contact the physician’s office if reaction symptoms occur. As with all allergenic extracts, severe systemic reactions may occur. In certain individuals, these life-threatening reactions may be fatal. Patients should be observed for 20 to 30 minutes following treatment, and emergency measures, as well as personnel trained in their use, should be immediately available in the event of a life-threatening reaction.

Sensitive patients may experience severe anaphylactic reactions resulting in respiratory obstruction, shock, coma and/or death. Patients with unstable asthma or steroid dependent asthmatics and patients with underlying cardiovascular disease are at greater risk to a fatal outcome from a systemic allergic reaction. If treated, these high risk patients should be started at lower (more conservative) doses and be progressed more slowly to a maintenance dose. Usually this is a lower dose than for those patients without these predispositions. (See DOSAGE AND ADMINISTRATION)

This product should not be injected intravenously. Deep subcutaneous routes have proven to be safe. See the warnings, precautions, adverse reactions and over-dosage sections below.

Patients receiving beta-blockers may not be responsive to epinephrine or inhaled bronchodilators. Respiratory obstruction not responding to parenteral or inhaled bronchodilators may require theophylline, oxygen, intubation and the use of life support systems. Parenteral fluid and/or plasma expanders may be utilized for treatment of shock. Adrenocorticosteroids may be administered parenterally or intravenously. Refer to the warnings, precautions and adverse reaction sections below.

Abelló

Port Washington, NY 11050

U.S. Government License No. 1256

DESCRIPTION

Center-Al® (Allergenic extracts, Alum Precipitated) is prepared from aqueous allergenic extracts by the formation of an aluminum hydroxide precipitated complex. It is supplied as a sterile suspension in multiple dose vials for subcutaneous injection. 0.4% Phenol is added as a preservative.

This product is compounded and diluted on a PNU basis. Extracts containing Short Ragweed Pollen also bear a labeled potency declaration in terms of Antigen E content.

CLINICAL PHARMACOLOGY

Numerous studies have confirmed Antigen E (AgE) as the major antigen associated with Short Ragweed pollinosis. In a well-controlled study, purified Antigen E was significantly superior to placebo in amelioration of symptoms associated with Short Ragweed pollinosis.¹ Therefore, it is essential that the physician be aware of AgE content of allergenic extracts administered for hyposensitization therapy.

Some studies have indicated that for most patients a cumulative Antigen E dosage of less than 0.1 unit is not immunizing (sufficient to stimulate specific IgG antibodies).² This, however, does not suggest that a 0.1 unit is a maximum tolerated dose. Most moderately sensitive patients may tolerate a dosage ten to fifty times greater. For exquisitely sensitive patients who cannot tolerate an immunizing dose of this preparation, the physician should consider immunotherapy with alternatives to conventional aqueous allergenic extract.

Alum precipitated bacterial and viral vaccines and alum precipitated toxoids have been effectively and routinely used in immunization injections for many years. The explanation usually given for the effect of such preparations is that the physical chemical absorption of an antigen onto an alum complex results in a slower release of the antigen with a consequent prolongation of the antigenic stimulus.

The treatment consists of the subcutaneous injection of gradually increasing doses of the allergens to which the patient is allergic. It has been demonstrated that this method of treatment induces an increased tolerance to the allergens responsible for the symptoms on subsequent exposure. Although the exact relationships between allergen, skin-sensitizing antibody (IgE) and the blocking antibody (IgG) have not been precisely established, clinically confirmed immunological studies have demonstrated the safety of Center-Al extracts and effectiveness in terms of symptom reduction and IgG response consistent with dose administered.³

In a controlled study with Center-Al Ragweed given pre-seasonally, patients were selected and matched by histamine release to Antigen E and assigned to treatment groups: Aqueous, Center-Al, and Placebo.³ All patients were highly sensitive to Ragweed Antigen E, reacting to <0.001 mcg Antigen E/mL as determined by intradermal skin testing. These patients received a pre-seasonal course of immunotherapy and achieved a mean cumulative dose of 52 units of Antigen E (27,365 PNU) in 13 to 19 injections. Starting doses in these patients were 10 PNU or approximately 0.02 units of AgE. This dosage was found to be significantly superior to Placebo as measured by symptom scores during the ragweed pollen season.

Although maximum tolerated doses for Center-Al expressed in AgE content have not specifically been studied, one investigator reported maximum tolerated doses with Center-Al ragweed at 2,000-5,000 PNU (4-10 units of Antigen E) with previously untreated patients.^9 At least three investigators using mixed (tall and short) ragweed extracts demonstrated a maximum tolerated peak dose of 2,000 to 10,000 PNU in 10-13 injections in moderately sensitive patients.^6,10-12 This was achieved by roughly doubling the dose in each successive injection at low dosages (<1,000 PNU) and if well tolerated, increasing the dosage approximately 50% until maximum tolerated dose for each patient was achieved.

Reaction rates for these patients were significantly lower than patients treated with aqueous extracts with the same or more conservative dosage regimen.^3,7,8,11

INDICATIONS AND USAGE

Hyposensitization (injection) therapy is a treatment for patients exhibiting allergic reactions to seasonal pollens, dust mites, molds, animal danders, and various other inhalants, in situations where the offending allergen cannot be avoided.

Prior to the initiation of therapy, clinical sensitivity should be established by careful evaluation of the patient’s history confirmed by diagnostic skin testing. Hyposensitization should not be prescribed for sensitivities to allergens which can be easily avoided.

CONTRAINDICATIONS

A patient should not be immunized against a substance which the patient has not demonstrated symptoms and/or tissue-fixed IgE antibodies as demonstrated by skin testing. Immunotherapy should not be attempted in patients with active asthma, severe respiratory obstruction, or cardiovascular disease.

There is some evidence, although inconclusive, that routine immunizations may exacerbate autoimmune diseases. Hyposensitization should be given cautiously to patients with this predisposition. The physician must weigh risk to benefit in these rare cases.

Patients with Alzheimer’s disease, Down’s syndrome and renal insufficiency are theoretically at risk from aluminum intake, including alum precipitated allergenic extracts.

WARNINGS

Patients should always be observed for at least 20-30 minutes after any injection. In the event of a marked systemic reaction, application of a tourniquet above the injection site and administration of 0.2 mL to 1.0 mL of Epinephrine injection (1:1,000) are recommended. Maximal recommended dose for children under 2 years of age is 0.3 mL. Maximal recommended dose for children between 2 and 12 years of age is 0.5 mL. The tourniquet is then gradually released. Patients under treatment with beta-blockers may be refractory to the usual dose of epinephrine.

PRECAUTIONS

Information For Patients:

Patients should be instructed to describe any active allergic symptoms such as rhinitis, wheezing, dyspnea, etc. prior to injection including any late reactions from previous administration Patients should be instructed to remain in the office for 20 to 30 minutes after injection to monitor for adverse reactions. Also, see ADVERSE REACTIONS and WARNINGS sections.

General:

1. Center-Al Allergenic Extracts, Alum Precipitated, are not to be used for intradermal testing.
2. Store at temperatures 2° and 8°C at all times, even during use.
3. DO NOT FREEZE. Freezing may cause agglomeration.
4. Shake vial thoroughly to disperse suspension prior to removal of the dose to be administered.
5. A separate sterile syringe and needle should be used for each individual patient, to prevent transmission of homologous serum hepatitis and other infectious agents from one person to another.
6. Injections are to be administered subcutaneously with the usual sterile precautions, preferably in the upper outer aspects of the arm, using a sterile tuberculin- type syringe and 25 or 26 gauge needle, 1⁄2 to 1⁄4 in length.
7. Avoid injecting intravenously. Pull back gently on syringe plunger and note if blood enters the syringe. If blood should enter the syringe, withdraw the needle and reinsert at another site, repeating the same precaution.
8. Allergenic extracts slowly become less potent with age. During the course of treatment, it may be necessary to continue therapy with a vial of extract bearing a later expiration date. The initial dose of the extract bearing the later expiration date should be lowered to a safe non-reaction-eliciting level, usually reducing the dosage of the first injection of the new vial 50-75% of the previous well tolerated dose of the older vial.
9. Subcutaneous nodules may develop at injection sites. The incidence of nodules increases with higher dosage of individual products and with extemporaneous mixtures at lower dosage. No single dose should provide more than 5,000 PNU whether as single allergen or mixture, nor should it exceed 0.5 mL in volume. If nodules occur, the highest single dose administered should be limited to a maximum of 0.2 mL (2,000 PNU).

DRUG INTERACTIONS:

Center-Al Allergenic Extracts, Alum Precipitated, are not to be mixed with any non-alum containing allergen(s) or with other types of alum precipitated products. Such mixing may free the alum-absorbed allergens.

Center-Al Allergenic Extracts, Alum Precipitated, should be diluted only with Sterile Diluent for Allergenic Extracts (Phenol-Saline) containing 0.9% Sodium Chloride, 0.4% Phenol. Use of other types of diluents may result in re-solution of some of the alum-complexed allergen thereby resulting in release of free aqueous extracts.

Patients receiving beta-blockers may not be responsive to epinephrine or an inhaled bronchodilator.

PREGNANCY - CATEGORY C:

Animal reproduction studies have not been conducted with Center-Al (Allergenic Extracts, Alum Precipitated). It is also not known whether Center-Al can cause fetal harm when administered to a pregnant woman or can affect reproduction capacity.

Controlled studies of hyposensitization with moderate to high doses of allergenic extracts during conception and all trimesters of pregnancy have failed to demonstrate any risk to the fetus or to the mother. However, on the basis of histamine’s known ability to contract the uterine muscle, the release of significant amounts of histamine from allergen exposure or hyposensitization overdose should be avoided on theoretical grounds. Therefore, allergenic extracts should be used cautiously in a pregnant woman and only if clearly needed.

PEDIATRIC USE:

Children can receive the same dose as adults, however, to minimize discomfort associated with dose volume it may be advisable to reduce the volume of the dose by one-half and administer the injection at two different sites.

NURSING MOTHERS:

It is not known if allergens administered subcutaneously appear in human milk. Because many drugs are excreted in human milk, caution should be exercised when allergenic extracts are administered to a nursing woman.

CARCINOGENESIS, MUTAGENESIS, IMPAIRMENT OF FERTILITY:

Studies in animals have not been performed.

ADVERSE REACTIONS

Local: Reactions at the site of injection may be immediate or delayed. Immediate wheal and erythema reactions are ordinarily of little consequence, but if very large may be the first manifestation of a systemic reaction. If large local reactions occur, the patient should be observed for systemic symptoms for which treatment is outlined below.

Delayed reactions start several hours after injection with local edema, erythema, itching or pain. They are usually at their peak at 24 hours and usually require no treatment. Antihistamine drugs may be administered orally.

The next therapeutic dose should be reduced to the dose which did not elicit a reaction, and subsequent doses increased more slowly, i.e., use of intermediate dilutions.

Systemic: It should be noted that anaphylaxis and deaths following the injection of mite and other extracts, including pollen extracts, have been reported by The British Committee on Safety in Medicine.^13 Fatalities from immunotherapy in the United States since 1945 have been extensively reviewed by Lockey, R.F., et al.^14 and also more recently by Reid, M.J., et al.^15 With careful attention to dosage and administration, such reactions occur infrequently, but it must be remembered that allergenic extracts are highly potent to sensitive individuals and OVERDOSE could result in anaphylactic symptoms. Therefore, it is imperative that physicians administering allergenic extracts understand and be prepared for the treatment of severe reactions.

Systemic reactions are characterized by one or more of the following symptoms: sneezing, mild to severe generalized urticaria, itching other than at the injection site, extensive or generalized edema, wheezing, asthma, dyspnea, cyanosis, tachycardia, lacrimation, marked perspiration, cough, hypotension, syncope and upper airway obstruction. Symptoms may progress to shock and death. Patients should always be observed for at least 20-30 minutes after any injection.

Volume expanders and vasopressor agents may be required to reverse hypotension. Inhalational bronchodilator and parenteral aminophylline may be required to reverse bronchospasm. Severe airway obstruction, unresponsive to bronchodilator, may require tracheal intubation.

In the event of a marked systemic reaction, application of a tourniquet above the injection site and administration of 0.2 mL to 1.0 mL of Epinephrine Injection (1:1,000) are recommended. Maximal recommended dose for children under 2 years of age is 0.3 mL. Maximal recommended dose for children between 2 and 12 years of age is 0.5 mL. The tourniquet is then gradually released.

The next therapeutic injection of extract should be reduced to the dose which did not elicit a reaction, and subsequent doses increased more slowly, i.e., use of intermediate dilutions.

Adverse Events should be reported via MedWatch (1-800-FDA-1088), Adverse Event Reporting, Food & Drug Administration, 5600 Fishers Lane, Rockville, MD 20852-9787.

DOSAGE AND ADMINISTRATION

The starting dose for immunotherapy is related directly to a patient’s sensitivity as determined by carefully executed percutaneous (prick/puncture) and intracutaneous (intradermal) skin testing with non-alum adsorbed allergenic extract. A general rule is to begin at 1/10 of the intradermal dose that produces sum of erythema of 50 mm (approximately a 2+ positive skin test reaction). Patient’s response to skin testing is graded on the basis of the size of the erythema and wheal. Refer to the diagnostic allergenic extract package enclosure for specific information.

TRANSFER OF PATIENTS FROM OTHER AQUEOUS
EXTRACTS TO CENTER-AL EXTRACTS

Patients may be transferred from other aqueous allergens to Center-Al Alum Precipitated Extracts during treatment. To avoid untoward reactions, it may be necessary to initiate treatment as though the patient were previously untreated. In transferring from standardized extracts, the more rapid rate of decline in activity of aqueous extract relative to alum precipitated extract must be considered in cautiously transferring patients to alum precipitated extract.

Caution should be observed since the Center-Al preparation may be more potent than the aqueous product.

TRANSFER OF PATIENTS FROM OTHER ALUM-COMPLEXED
EXTRACTS TO CENTER-AL EXTRACTS

Patients may be transferred from other alum-complexed allergenic extracts to Center-Al Alum Precipitated extracts. In order to avoid untoward reactions, it is recommended that previous therapy be disregarded and therapy with Center-Al be initiated as though the patient were previously untreated. The first dose of Center-Al should be related to the patient’s sensitivity, determined by history and confirmed by skin testing. CAUTION: Center-Al Alum Precipitated extracts should not be mixed with other alum precipitated or aqueous extracts.

PRE-SEASONAL AND PERENNIAL METHOD OF TREATMENT

The use of Center-Al Allergenic extract, Alum Precipitated, in the treatment of patients by the pre-seasonal method should be started 10 to 12 weeks prior to the usual onset of symptoms. Therapy should be initiated early enough to permit a graduated series of doses at weekly intervals. It is recommended that the larger doses be spaced 2 to 3 weeks apart and that the top dose be reached prior to the season.

Increased tolerance acquired through hyposensitization can vary from a few to several months. To assure prolongation of this acquired tolerance, perennial or year-round treatment is recommended. Some physicians continue therapy into or through the season by repeating a reduced MAINTENANCE dose at 4 to 6 week intervals.

SUGGESTED DOSAGE SCHEDULE

A treatment schedule is related directly to the patient’s degree of sensitivity, determined initially by clinical history and skin testing, and continuously by response to therapeutic doses. Thus, an individual treatment schedule for each patient must be established during the course of therapy. Maximum protection can be obtained with a dosage kept constantly below the patient’s limit of tolerance. Every precaution should be taken to avoid a systemic or generalized reaction which in addition to being dangerous, may depress rather than increase the patient’s tolerance.

FOR ALL PREPARATIONS (EXCEPT SHORT RAGWEED AND
MIXED SHORT AND TALL RAGWEED)

Labeled Antigen E content of extracts containing Short Ragweed at a weight/volume concentration more dilute than 1:10 may have been obtained by calculation from the Antigen E assay value of a more concentrated extract that was analyzed, officially released by the Office of Biologics, and subsequently diluted.

Below is listed a suggested dosage schedule for Pre-Seasonal Treatment. A column has been left blank for AgE dosage of short ragweed containing extracts.

Note: For extracts of short ragweed or equal part mixture of Short and Tall Ragweed refer to AgE dosage schedule. The AgE content for those products is indicated on the vial label. The physician may use the formula below to determine the AgE dosage for each injection.

AgE dosage can be monitored by using the formula:

Labeled AgE X dose in PNU = dose in AgE Labeled PNU/mL

Note: Suggested dosage schedules which follow have not been subjected to adequate and well controlled trials to establish their safety and efficacy.

Dose No. | Vial Strength | Volume Injected | PNU Per Dose | AgE Dose
1 | 100 PNU/mL | 0.1 mL | 10
2 | 100 PNU/mL | 0.2 mL | 20
3 | 100 PNU/mL | 0.5 mL | 50
4 | 1,000 PNU/mL | 0.1 mL | 100
5 | 1,000 PNU/mL | 0.25 mL | 250
6 | 1,000 PNU/mL | 0.5 mL | 500
7 | 10,000 PNU/mL | 0.1 mL | 1,000
8 | 10,000 PNU/mL | 0.2 mL | 2,000
9 | 10,000 PNU/mL | 0.3 mL | 3,000
10 | 10,000 PNU/mL | 0.4 mL | 4,000
11 | 10,000 PNU/mL | 0.5 mL | 5,000

MAINTENANCE DOSE:

10,000 PNU/mL 0.5 mL 5,000

NO SINGLE DOSE SHOULD EXCEED 5,000 PNU. For continuing therapy with extracts containing Short Ragweed, see following section on Dosage Adjustments.

SHORT RAGWEED EQUAL PARTS MIXES OF SHORT AND TALL
RAGWEED (DOSAGE BASED ON ANTIGEN CONTENT)

Suggested dosage schedule for Short Ragweed and Equal Part Mixture of Short and Tall Ragweed:

Dose No | AgE Units/mL | Volume Injected | AgE Per Dose
1 | 0.4 | 0.1 | 0.04
2 | 0.4 | 0.2 | 0.08
3 | 0.4 | 0.5 | 0.2
4 | 4 | 0.1 | 0.4
5 | 4 | 0.25 | 1.0
6 | 4 | 0.5 | 2.0
7 | 40 | 0.1 | 4.0
8 | 40 | 0.2 | 8.0
9 | 40 | 0.3 | 12
10 | 40 | 0.4 | 16
11 | 40 | 0.5 | 20

MAINTENANCE DOSE:
40 | 0.5 | 20
80 | 0.25 | 20

NO SINGLE DOSE SHOULD EXCEED 20 UNITS

DOSAGE ADJUSTMENTS
(FOR PRODUCTS CONTAINING SHORT RAGWEED)

AgE is important in adjusting dosage of Short Ragweed extracts to accurately transfer a patient from older extracts to fresher material. In such cases, the dosage of AgE should be considered in addition to the protein nitrogen units. Antigen E concentration continuously declines in Short Ragweed Pollen extracts at a rate that varies with the formulation of the product. Aqueous extracts retain Antigen E potency less effectively than 50% glycinerated or Alum Precipitated extracts. Antigen E is most stable in freeze-dried extracts. These differences are reflected in the expiration date declared on the vial label. The continuous decline should be considered. Also, where Ragweed is a component of an allergen mixture, clinical response to the other components must be considered in adjustment of dosage based on AgE content alone.

CAUTION: A small percent of individuals allergic to Short Ragweed are more sensitive to minor antigens such as Ra3 and Ra5 than AgE. There is no correlation between the amount of these antigens and either AgE or PNU content.

HOW SUPPLIED

Therapeutic Center-Al Allergenic Extracts, Alum Precipitated, are supplied in 10 mL and 30 mL vials, in concentrations of 10,000 PNU/mL and 20,000 PNU/mL. Prescription treatment sets for individual patients are also available. Center-Al must be stored continuously at 2° to 8°C. DO NOT FREEZE. Diluent: Sterile Diluent for allergenic extracts (Phenol-Saline) is provided in vials of 4.5 mL, 9.0 mL, and 30 mL.

STORAGE: To maintain stability of allergenic extracts, proper storage conditions are essential. Bulk concentrates and diluted extracts are to be stored at 2° to 8°C even during use. Bulk or diluted extracts are not to be frozen. Do not use after the expiration date shown on the vial label.

REFERENCES

1. Norman, P.S.et.al.: Immunotherapy of hayfever with ragweed antigen E. Comparisons with whole pollen extract and placebo. J. Allergy 42:93, 1968.
2. Van Metre, T.E. et. al.: A controlled study of the effectiveness of the Rinkel method of immunotherapy for ragweed pollen hayfever. J. Allergy Clin. Immunol. 61:384, 1978.
3. Norman, P.S. and Lichtenstein, L.M.: Comparisons of alum precipitated and unprecipitated aqueous ragweed pollen extracts in the treatment of hayfever. J. Allergy Clin. Immunol. 61:384, 1978.
4. Ransom, J.H.: Clinical and laboratory evaluation of alum precipitated ragweed extract. Ann. Allergy 28:22, 1970.
5. Ransom, J.H.: Frequency of reactions to alum precipitated ragweed extract. Ann. Allergy 29:635, 1971.
6. Lazar, H. and Leoffler, J.A.: Evaluation of an alum precipitated mixed ragweed antigen: a three-year study. Ann. Allergy 28:214, 1970.
7. Norman, P.S., Winkenwerder, W.L., and Lichtenstein, L.M.: Trials of alum precipitated pollen extracts in the treatment of hayfever. J. Allergy Clin. Immunol. 50:31, 1972.
8. Nelson, H.S.: Long-term immunotherapy with aqueous and alum precipitated grass extracts. Ann. Allergy 45:333, 1980.
9. Norman,. P.S.: The role of In-Vitro assays in the evaluation of immunotherapy. Recent Advances in Immunotherapy. Port Washington, NY 1973.
10. Lazar, H.: Clinical presentation covering 6 years of observation. Recent Advances in Immunotherapy. Port Washington, NY 1973.
11. Haynes, J.T.: A clinical study of 23 ragweed sensitive patients. Recent Advances in Immunotherapy. Port Washington, NY 1973.
12. Ransom, J.H.: Ragweed patient study. Recent Advances in Immunotherapy. Port Washington, NY 1973.
13. Committee on the Safety of Medicines. CSM update: desensitizing vaccines. Brit. Med. J. 1986; 293:948.
14. Lockey, R.F. et al.: Fatalities from immunotherapy (IT) and skin testing (ST). J. Allergy Clin. Immunol. 1987; 79:660.
15. Reid, M.J. et al.: Survey of fatalities from skin testing and immunotherapy. 1985-1989. J. Allergy Clin. Immunol. 1993; 92:6.

Revision: June 2013

© ALK-Abello, Inc. 2013

168H

Distributed in Canada by:
ALK-Abello Pharmaceuticals, Inc.
#35-151 Brunel Road Mississauga, Ontario
Canada L4Z 2H6

PRINCIPAL DISPLAY PANEL

Allergenic Extract, Alum Precipitated
Center-AL
DIN 00648922
30 mL Sterile Multiple Dose Vial